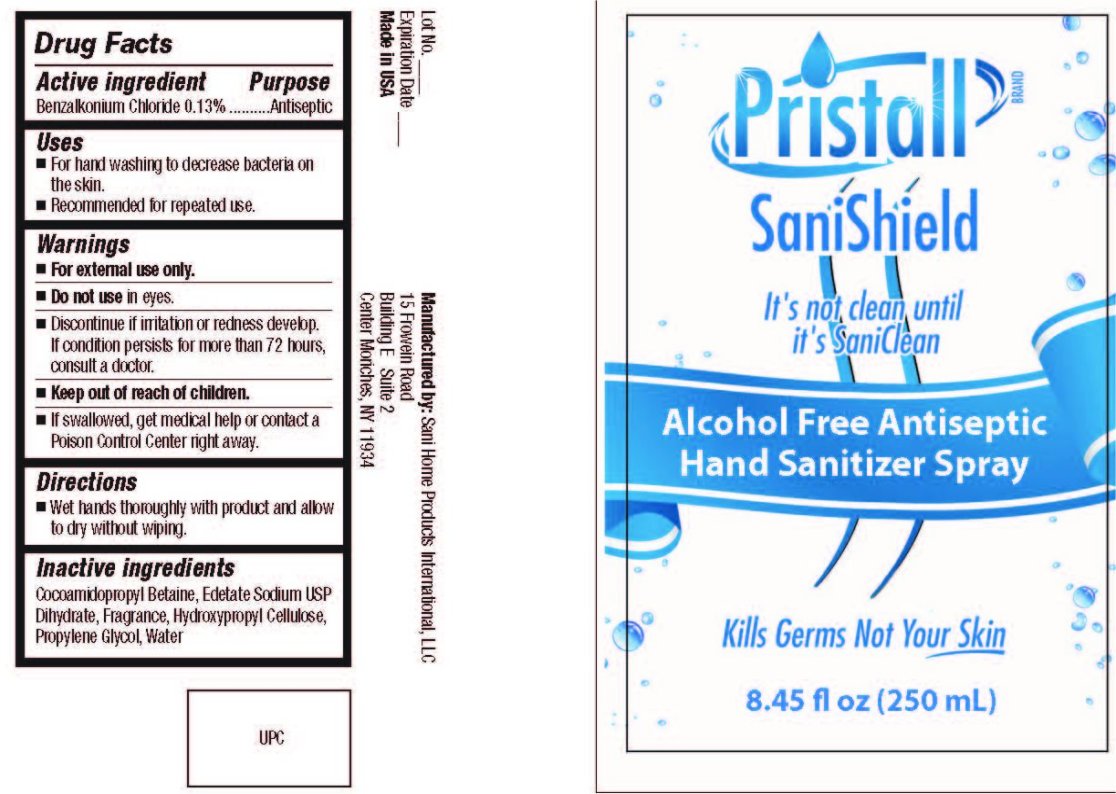 DRUG LABEL: Pristall SaniShield Alcohol Free Antiseptic Hand Sanitizer
NDC: 50757-250 | Form: SPRAY
Manufacturer: Sani Home Products International LLC
Category: otc | Type: HUMAN OTC DRUG LABEL
Date: 20100323

ACTIVE INGREDIENTS: BENZALKONIUM CHLORIDE 0.13 mL/100 mL
INACTIVE INGREDIENTS: COCAMIDOPROPYL BETAINE; EDETATE SODIUM; HYDROXYPROPYL CELLULOSE; PROPYLENE GLYCOL; WATER

Pristall SaniShield Alcohol Free Antiseptic Hand Sanitizer Spray

Drug Facts

Active Ingredient Purpose

Benzalkonium Chloride 0.13 percent Antiseptic

Uses

For hand washing to decrease bacteria on the skin. Recommended for repeated use.

Warnings

For external use only.

Do not use in eyes.

STOP USE

Discontinue if irritation or redness develop. If condition persists for more than 72 hours, consult a doctor.

Keep out of reach of children.

WARNINGS AND PRECAUTIONS

If swallowed, get medical help or contact a Poison Control Center right away

Directions

Wet hands thoroughly with product and allow to dry without wiping.

Inactive Ingredients

Cocoamidopropyl Betaine, Edetate Sodium USP Dihydrate, Fragrance, Hydroxypropyl Cellulose, Propylene Glycol, Water

DESCRIPTION

Lot No. Expiration Date Made in USA Manufactured by: Sani Home Products International, LLC 15 Frowein Road Buiding E Suite 2 Center Moriches, NY 11934

PACKAGE LABEL

Pristall SaniShield It's not clean until it's SaniClean Alcohol Free Antiseptic Hand Sanitizer Spray Kills Germs Not Your Skin 8.45 fl oz (250 ml)